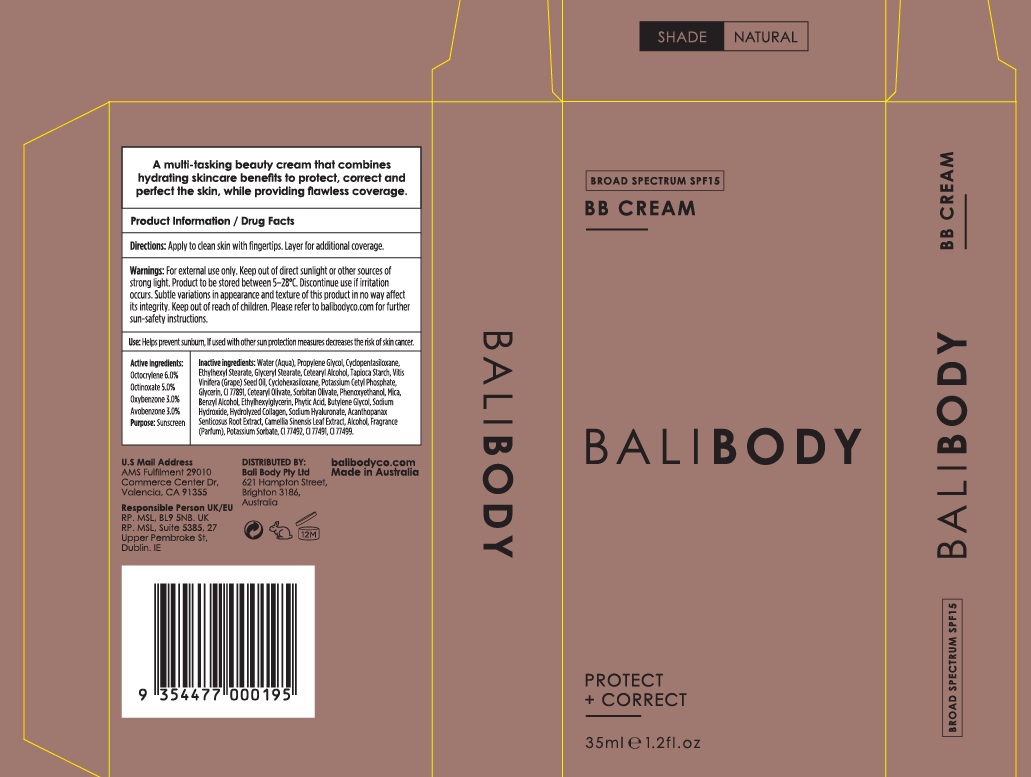 DRUG LABEL: Bali Body BB Cream SPF 15 Natural
NDC: 70630-0029 | Form: CREAM
Manufacturer: Bali Body Pty Ltd
Category: otc | Type: HUMAN OTC DRUG LABEL
Date: 20241021

ACTIVE INGREDIENTS: OCTOCRYLENE 60 mg/1 mL; OCTINOXATE 50 mg/1 mL; AVOBENZONE 30 mg/1 mL; OXYBENZONE 30 mg/1 mL
INACTIVE INGREDIENTS: FYTIC ACID; PROPYLENE GLYCOL; WATER; ETHYLHEXYL STEARATE; CYCLOMETHICONE 5; GLYCERYL MONOSTEARATE; GRAPE SEED OIL; STARCH, TAPIOCA; CYCLOMETHICONE 6; CETOSTEARYL ALCOHOL; POTASSIUM CETYL PHOSPHATE; CETEARYL OLIVATE; GLYCERIN; HYALURONATE SODIUM; GREEN TEA LEAF; ELEUTHERO; SORBITAN OLIVATE; BUTYLENE GLYCOL; ALCOHOL; SODIUM HYDROXIDE; PHENOXYETHANOL; BENZYL ALCOHOL; ETHYLHEXYLGLYCERIN; POTASSIUM SORBATE; MICA; FERRIC OXIDE YELLOW; FERRIC OXIDE RED; FERROSOFERRIC OXIDE; TITANIUM DIOXIDE

Bali Body BB Cream SPF 15 Natural

Directions:

Apply to clean skin with fingertrips. Layer for additional coverage.

Warnings:

For external use only. Keep out of direct sunlight or other sources of strong light. Product to be stored between 5-28°C. Discontinue use if irritation occurs. Subtle variations in appearance and texture of this product in no way affect its integrity.

Keep out of reach of children.

Please refer to balibodyco.com for further sun-safety instructions.

Use:

Helps prevent sunburn, If used with other sun protection measures decreases the risk of skin cancer.

Active ingredients:

Octocrylene 6.0%
Octinoxate 5.0%
Avobenzone 3.0%
Oxybenzone 3.0%

Purpose:

Sunscreen

Inactive ingredients:

Water (Aqua), Propylene Glycol, Cyclopentasiloxane, Ethylhexyl Stearate, Glyceryl Stearate, Cetearyl Alcohol, Tapioca Starch, Vitis Vinifera (Grape) Seed Oil, Cyclohexasiloxane, Potassium Cetyl Phosphate, Glycerin, CI 77891, Cetearyl Olivate, Sorbitan Olivate, Phenoxyethanol, Mica, Benzyl Alcohol, Ethylhexylglycerin, Phytic Acid, Butylene Glycol, Sodium Hydroxide, Hydrolyzed Collagen, Sodium Hyaluronate, Acanthopanax Senticosus Root Extract, Camellia Sinensis Leaf Extract, Alcohol, Fragrance (Parfum), Potassium Sorbate, CI 77492, CI 77491, CI 77499.